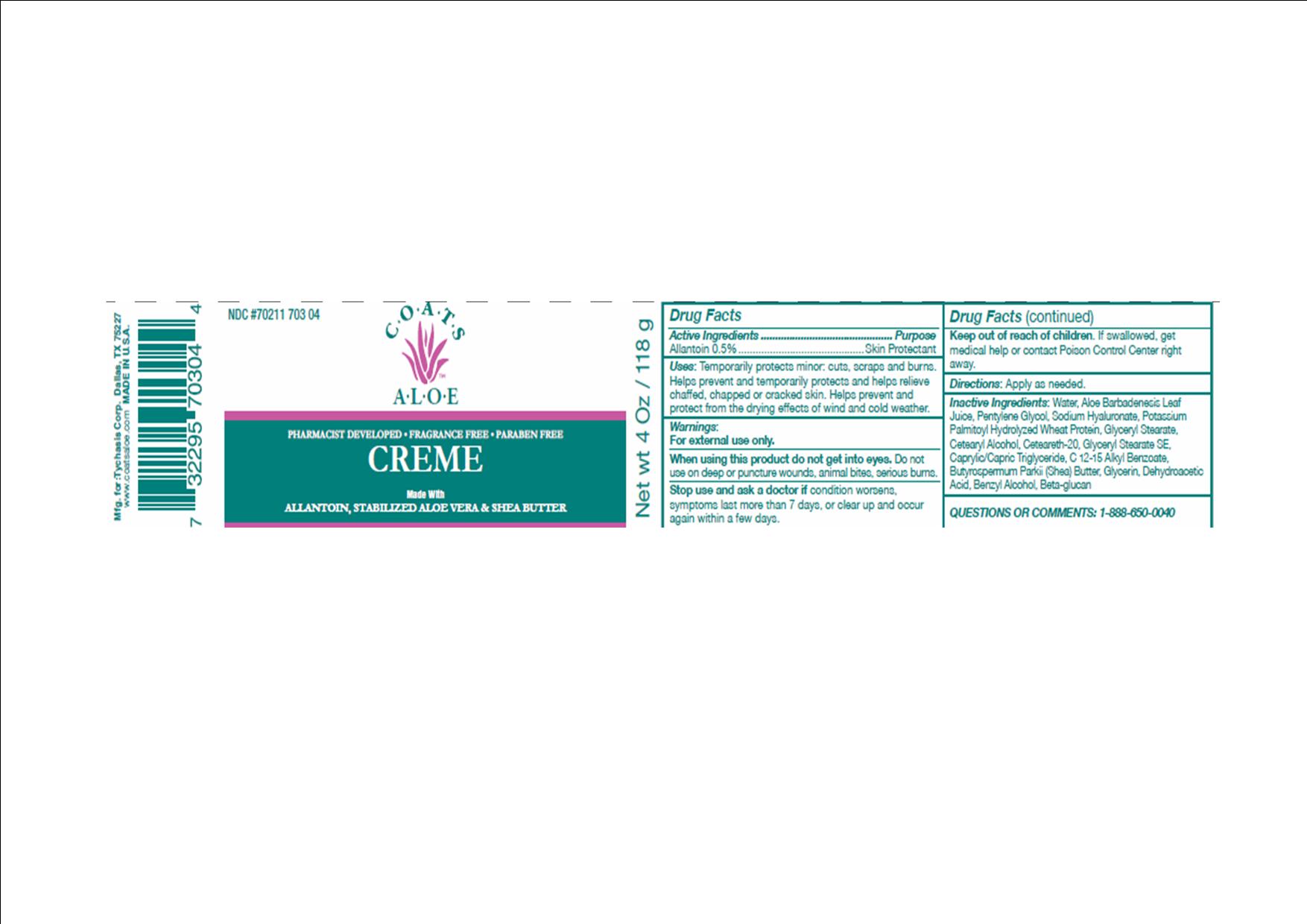 DRUG LABEL: COATS ALOE
NDC: 70211-703 | Form: CREAM
Manufacturer: TYCHASIS CORPORATION
Category: otc | Type: HUMAN OTC DRUG LABEL
Date: 20241028

ACTIVE INGREDIENTS: ALLANTOIN 0.5 mg/100 g
INACTIVE INGREDIENTS: WATER; ALOE VERA LEAF; CAPRYLIC/CAPRIC/LAURIC TRIGLYCERIDE; PENTYLENE GLYCOL; HYALURONATE SODIUM; SHEA BUTTER; GLYCERIN; POTASSIUM PALMITATE; BENZYL ALCOHOL; DEHYDROACETIC ACID; HYDROLYZED WHEAT PROTEIN (ENZYMATIC, 3000 MW); GLYCERYL STEARATE SE; ALKYL (C12-15) BENZOATE

COATS ALOE CREME

Active Ingredient:

Allantoin 0.5%

Purpose:

Skin Protectant

Warnings:

For external use only.

Do not get into eyes.

Stop use and ask doctor if:

Stop use and ask a doctor if condition worsens, symptoms last more than 7 days, or clear up and occur again within a few days.

Indications and Usage:

Temporarily protects minor:

- cuts
- scrapes
- burns

Helps prevent and temporarily protects and helps relieve chaffed, chapped or cracked skin.

Helps prevent and protect from the drying effects of wind and cold weather.

Caution:

Do not use on deep puncture wounds, animal bites, serious burns.

Keep out of reach of children:

If swallowed, get medical help or contact a poison control right away.

Directions:

Apply as needed.

Inactive Ingredients:

water, aloe barbadenesis leaf juice, caprylic/capric triglyceride, cetyl alcohol, potassium palmityl hydrolyzed wheat protein, glyceryl stearate, pentylene glycol, butryospermum parkii (shea) butter, C12-15 alkyl benzoate, glycerin, beta-glucan, sodium hyaluronate, glyceryl stearate SE, ceteareth-20, dehydroacetic acid, benzyl alcohol

Questions:

Toll free number 888-650-0040